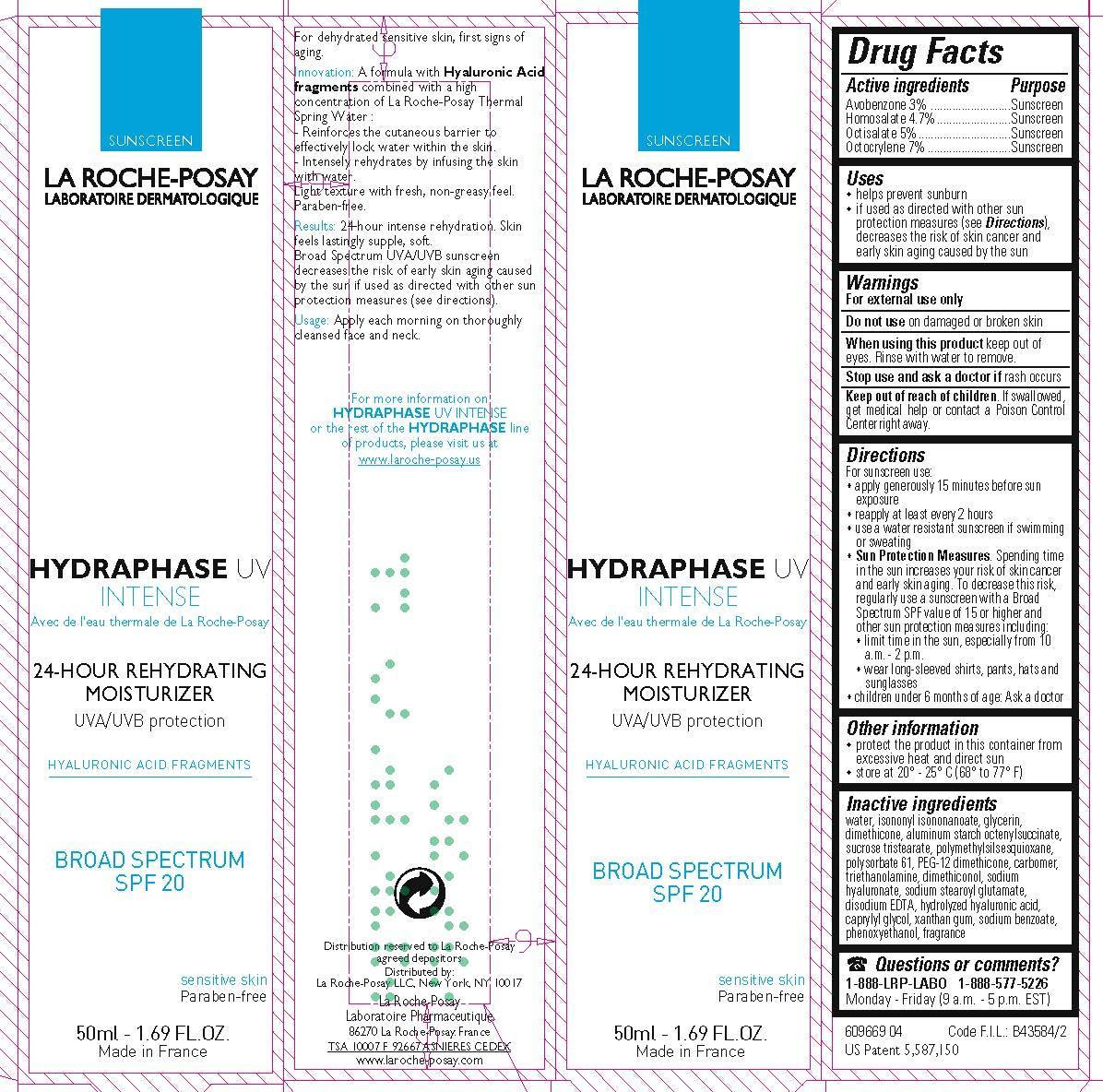 DRUG LABEL: La Roche Posay Laboratoire Dermatologique Hydraphase UV Intense Moisturizer Broad Spectrum SPF 20 Sunscreen
NDC: 49967-126 | Form: LOTION
Manufacturer: L'Oreal USA Products Inc
Category: otc | Type: HUMAN OTC DRUG LABEL
Date: 20240101

ACTIVE INGREDIENTS: AVOBENZONE 30 mg/1 mL; HOMOSALATE 47 mg/1 mL; OCTISALATE 50 mg/1 mL; OCTOCRYLENE 70 mg/1 mL
INACTIVE INGREDIENTS: WATER; ISONONYL ISONONANOATE; GLYCERIN; DIMETHICONE; ALUMINUM STARCH OCTENYLSUCCINATE; SUCROSE TRISTEARATE; POLYMETHYLSILSESQUIOXANE (11 MICRONS); POLYSORBATE 61; PEG-12 DIMETHICONE; CARBOMER HOMOPOLYMER TYPE C (ALLYL PENTAERYTHRITOL CROSSLINKED); TROLAMINE; DIMETHICONOL (100000 CST); HYALURONATE SODIUM; SODIUM STEAROYL GLUTAMATE; EDETATE DISODIUM; CAPRYLYL GLYCOL; XANTHAN GUM; SODIUM BENZOATE; PHENOXYETHANOL

Drug Facts

Active ingredients

Avobenzone 3%

Homosalate 4.7%

Octisalate 5%

Octocrylene 7%

Purpose

Sunscreen

Uses

- helps prevent sunburn

- if used as directed with other sun protection measures (see Directions), decreases the risk of skin cancer and early skin aging caused by the sun

Warnings

For external use only

Do not use

on damaged or broken skin

When using this product

keep out of eyes. Rinse with water to remove.

Stop use and ask a doctor if

rash occurs

Keep out of reach of children.

If swallowed, get medical help or contact a Poison Control Center right away.

Directions

For sunscreen use:

● apply generously 15 minutes before sun exposure

● reapply at least every 2 hours

● use a water resistant sunscreen if swimming or sweating

● Sun Protection Measures. Spending time in the sun increases your risk of skin cancer and early skin aging. To decrease this risk, regularly use a sunscreen with a Broad Spectrum SPF value of 15 or higher and other sun protection measures including:

● limit time in the sun, especially from 10 a.m. – 2 p.m.

● wear long-sleeved shirts, pants, hats, and sunglasses

● children under 6 months of age: Ask a doctor

Other information

protect the product in this container from excessive heat and direct sun

Inactive ingredients

water, isononyl isononanoate, glycerin, dimethicone, aluminum starch octenylsuccinate, sucrose tristearate, polymethylsilsesquioxane, polysorbate 61, PEG-12 dimethicone, carbomer, triethanolamine, dimethiconol, sodium hyaluronate, sodium stearoyl glutamate, disodium EDTA, hydrolyzed hylauronic acid, caprylyl glycol, xanthan gum, sodium benzoate, phenoxyethanol, fragrance

Questions or comments?

1-888-LRP-LABO 1888-577-5226

Monday - Friday (9 a.m. - 5 p.m. EST)